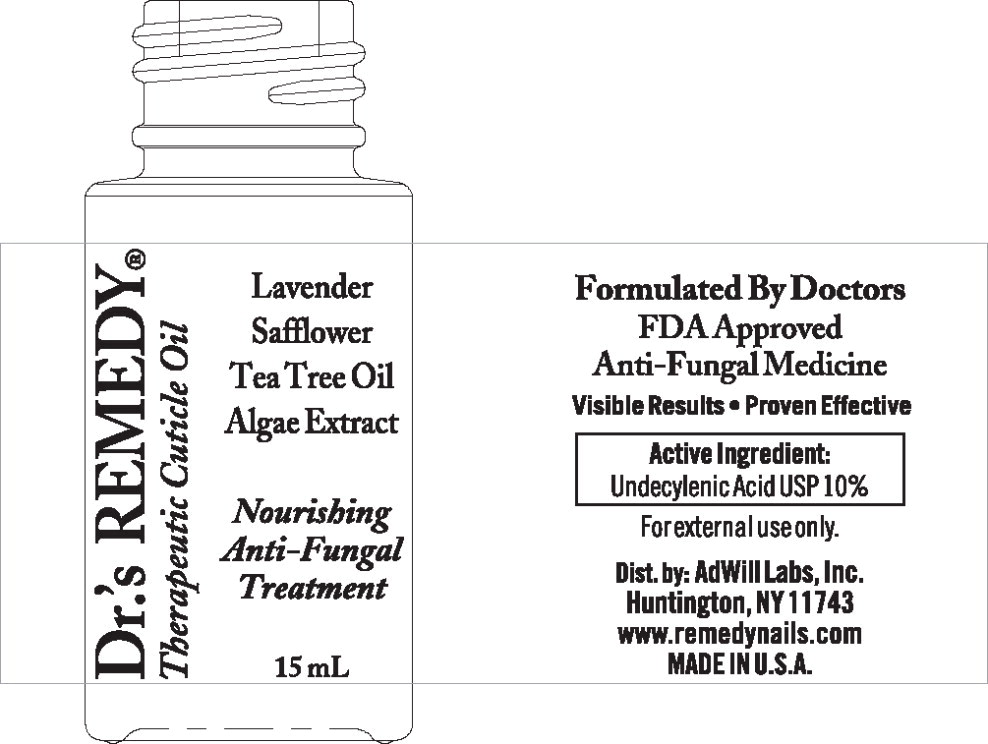 DRUG LABEL: Remedy Nails
NDC: 72222-224 | Form: LOTION
Manufacturer: Adwill Labs Inc
Category: otc | Type: HUMAN OTC DRUG LABEL
Date: 20241107

ACTIVE INGREDIENTS: UNDECYLENIC ACID 85 mg/1 mL
INACTIVE INGREDIENTS: MINERAL OIL; ISOPROPYL MYRISTATE; SAFFLOWER OIL; TEA TREE OIL; GRAPE SEED OIL; .ALPHA.-TOCOPHEROL ACETATE; LAVENDER OIL

DRUG FACTS

ACTIVE INGREDIENT:

Undecylenic Acid USP 10%

PURPOSE:

Anti-Fungal

USES:

Treats cuticle and skin fungal infections.

- Heals and moisturizes cuticles and skin.
- Athlete's foot treatment.
- Relieves itching, burning and cracking.

WARNINGS: FOR EXTERNAL USE ONLY.

Keep out of reach of children.

- Consult your doctor if you are pregnant before using this product.
- It is not known whether this drug passes into breast milk.
- Consult your doctor before breast feeding.
- If swallowed, call Poison Control Center immediately.

STOP USE AND ASK A DOCTOR IF:

Irritation occurs.

- No improvement within 2 weeks.

DIRECTIONS:

Wash and dry affected area.

- Apply a thin layer over affected area twice daily or as directed by a doctor.
- Apply enough medication to cover the affected area and surrounding skin.
- Wash hands after use.
- For maximum results, use twice daily or as instructed.
- Discontinuing use of this medication may allow recurrence of infection.
- If condition persists, consult your doctor.

CAUTION:

Do not accept if safety seal is broken or missing.

- Store at room temperature 60-85F.
- Keep in tight, light resistant container.

ALLERGIC REACTIONS:

Contact doctor if unusual reactions to this medicine occur.

- This product does not contain FD&C Yellow #5 or FD&C Yellow #6.

INACTIVE INGREDIENTS:

Mineral Oil, Isopropyl Myristate, Lavandula Angustifolia (Lavender) Oil, Linalool, Carthamus Tinctorius (Safflower) Seed Oil, Limonene, Aleurites Moluccana (Kukui) Seed Oil, Melaleuca Alternifolia (Tea Tree) Leaf Oil, Tocopheryl Acetate, Vitis Vinifera (Grape) Seed Oil, Algae Extract.

Principal Display Panel - 15 mL Bottle Label

Dr.'s REMEDY®
Therapeutic Cuticle Oil

Lavender
Safflower
Tea Tree Oil
Algae Extract

Nourishing
Anti-Fungal
Treatment

15mL